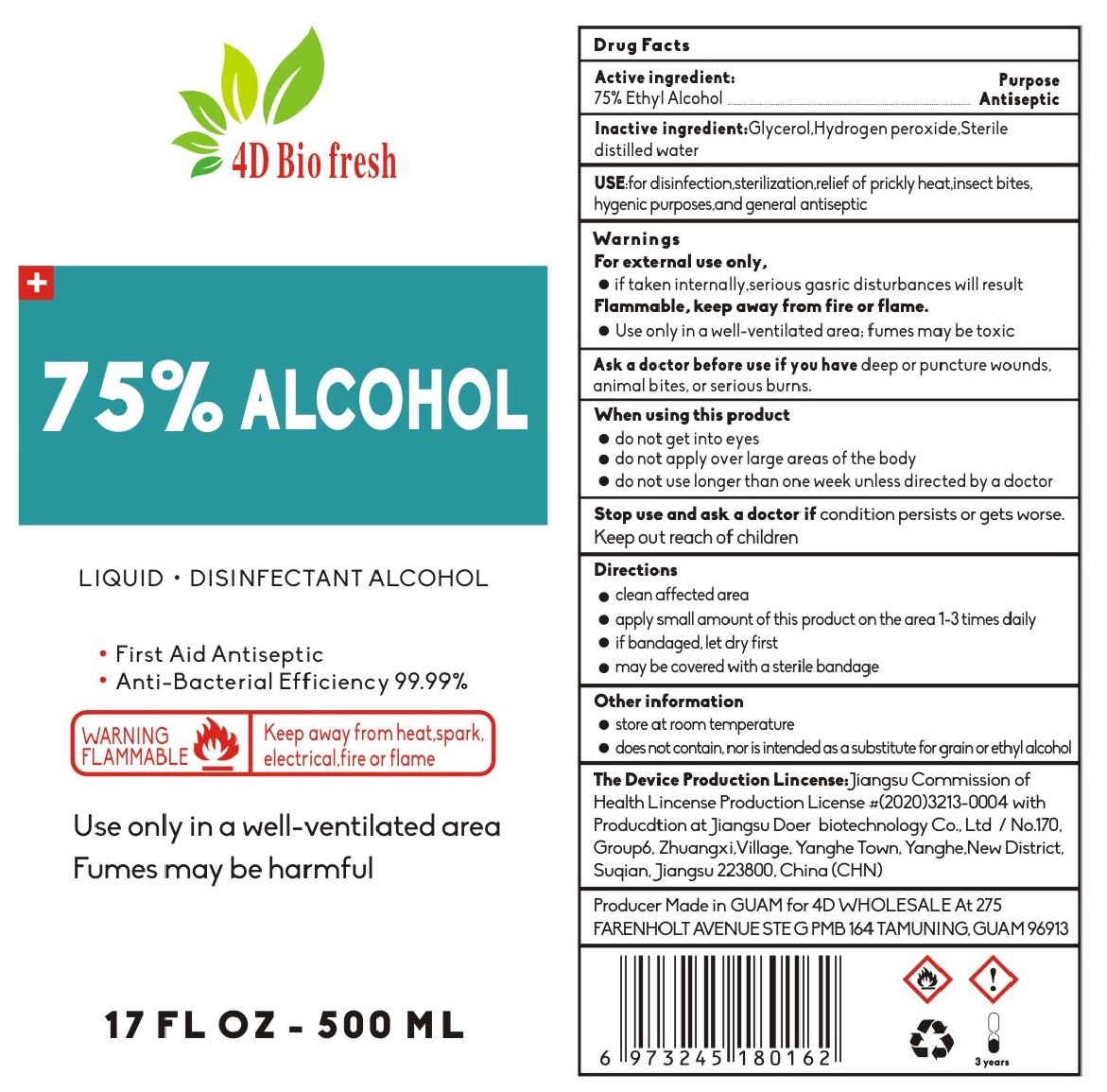 DRUG LABEL: Hand Sanitizer
NDC: 55449-075 | Form: LIQUID
Manufacturer: Jiangsu Doer biotechnology Co., Ltd
Category: otc | Type: HUMAN OTC DRUG LABEL
Date: 20211029

ACTIVE INGREDIENTS: ALCOHOL 75 mL/100 mL
INACTIVE INGREDIENTS: GLYCERIN; HYDROGEN PEROXIDE; WATER

Hand Sanitizer 55449-075-01 500ml 55449-075-02 946ml

This is a hand sanitizer manufactured according to the Temporary Policy for Preparation of Certain Alcohol-Based Hand Sanitizer Products During the Public Health Emergency (CoViD-19); Guidance for Industry.

The hand sanitizer is manufactured using only the following United States Pharmacopoeia (USP) grade ingredients in the preparation of the product (percentage in final product formulation) consistent with World Health Organization (WHO) recommendations:

1. Isopropyl Alcohol (75%, v/v) in an aqueous solution denatured according to Alcohol and Tobacco Tax and Trade Bureau regulations in 27 CFR part 20.
2. Glycerol (1.45% v/v).
3. Hydrogen peroxide (0.125% v/v).
4. Sterile distilled water or boiled cold water.

The firm does not add other active or inactive ingredients. Different or additional ingredients may impact the quality and potency of the product.

Active Ingredient(s)

Alcohol 75% v/v. Purpose: Antiseptic

Purpose

Antiseptic, Hand Sanitizer

Use

USE: for disinfection, sterilization. relief of prockly heat. insect bites, hygenic purposes and general antiseptic.

Warnings

For external use only. if taken internally serious gasric disturbances will result.

Flammable. Keep away from heat or flame. Use only in a well-ventilated area; fumes may be toxic.

Do not use

- in children less than 2 months of age
- on open skin wounds

WHEN USING

do not get into eyes.

do not apply over large areas of the body.

do not use longer than one week unless directed by a doctor

Stop use and ask a doctor if condition persists or gets worse. Keep out reach of children.

Keep out of reach of children. If swallowed, get medical help or contact a Poison Control Center right away.

Directions

- clean affected area.
- apply small amount of this product on the area 1-3 times dailly.
- if bandaged let dry first.
- may be covered with a sterile bandage.

Other information

- Store between 15-30C (59-86F)
- Avoid freezing and excessive heat above 40C (104F)

Inactive ingredients

glycerin, hydrogen peroxide, purified water USP

Package Label - Principal Display Panel

500 ml NDC:55449-075-01